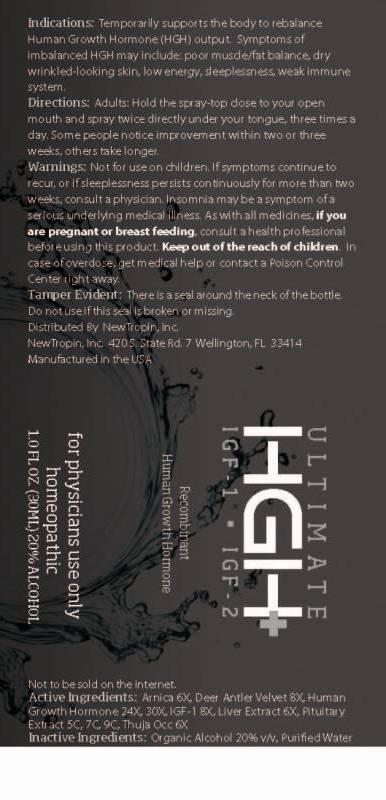 DRUG LABEL: Ultimate High IGF 1 IGF 2
NDC: 45046-0001 | Form: LIQUID
Manufacturer: NewTropin, Inc.
Category: homeopathic | Type: HUMAN OTC DRUG LABEL
Date: 20130325

ACTIVE INGREDIENTS: ARNICA MONTANA 6 [hp_X]/1 mL; CERVUS ELAPHUS VELVET 8 [hp_X]/1 mL; BEEF LIVER 6 [hp_X]/1 mL; SOMATROPIN 24 [hp_X]/1 mL; MECASERMIN 8 [hp_X]/1 mL; BOS TAURUS PITUITARY GLAND 5 [hp_C]/1 mL; THUJA OCCIDENTALIS LEAF 6 [hp_X]/1 mL
INACTIVE INGREDIENTS: WATER; ALCOHOL

Drug Facts

ACTIVE INGREDIENTS

Arnica Montana 6X, Deer Antler Velvet 8X, Hepar Bovinum 6X, HGH 24X, 30X, IGF 1 8X, Pituitary Bovinum 5C, 7C, 9C, Thuja Occidentalis 6X

INDICATIONS

Temporarily supports the body to rebalance Human Growth Hormone (HG) output. Symptoms of imbalanced HGH may include: poor muscle/fat balance, dry wrinkled looking skin, low energy, sleeplessness, weak immune system.

WARNINGS

Not for use on children. If symptoms continue to recur, or if sleeplessness persists continuously for more than two weeks, consult a physician. Insomnia may be a symptom of a serious underlying medical illness. As with all medicines, if you are pregnant or breast feeding, consult a health professional before using this product. Keep out of the reach of children. In case of overdose get medical help or contact a Poison Control Center right away.

Tamper Evident: There is a seal around the neck of the bottle. Do not use if this seal is broken or missing.

DIRECTIONS

Adults: Hold the spray-top close to your open mouth and spray twice directly under your tongue, three times a day. Some people notice improvement within two or three weeks, others take longer.

INACTIVE INGREDIENTS

Purified Water, Ethanol 20%

KEEP OUT OF REACH OF CHILDREN

In case of overdose get medical help or contact a Poison Control Center right away.

INDICATIONS AND USAGE

Temporarily supports the body to rebalance Human Growth Hormone (HG) output. Symptoms of imbalanced HGH may include: poor muscle/fat balance, dry wrinkled looking skin, low energy, sleeplessness, weak immune system.

QUESTIONS

NewTropin, Inc 420 S. State Rd, 7 Wellington, FL 33414

PACKAGE LABEL

ULTIMATE

HGH

IGF 1 IGF 2

Recombinant

Human Growth Hormone

for physicians use only

homeopathic

1.0 FL OZ (30ML)